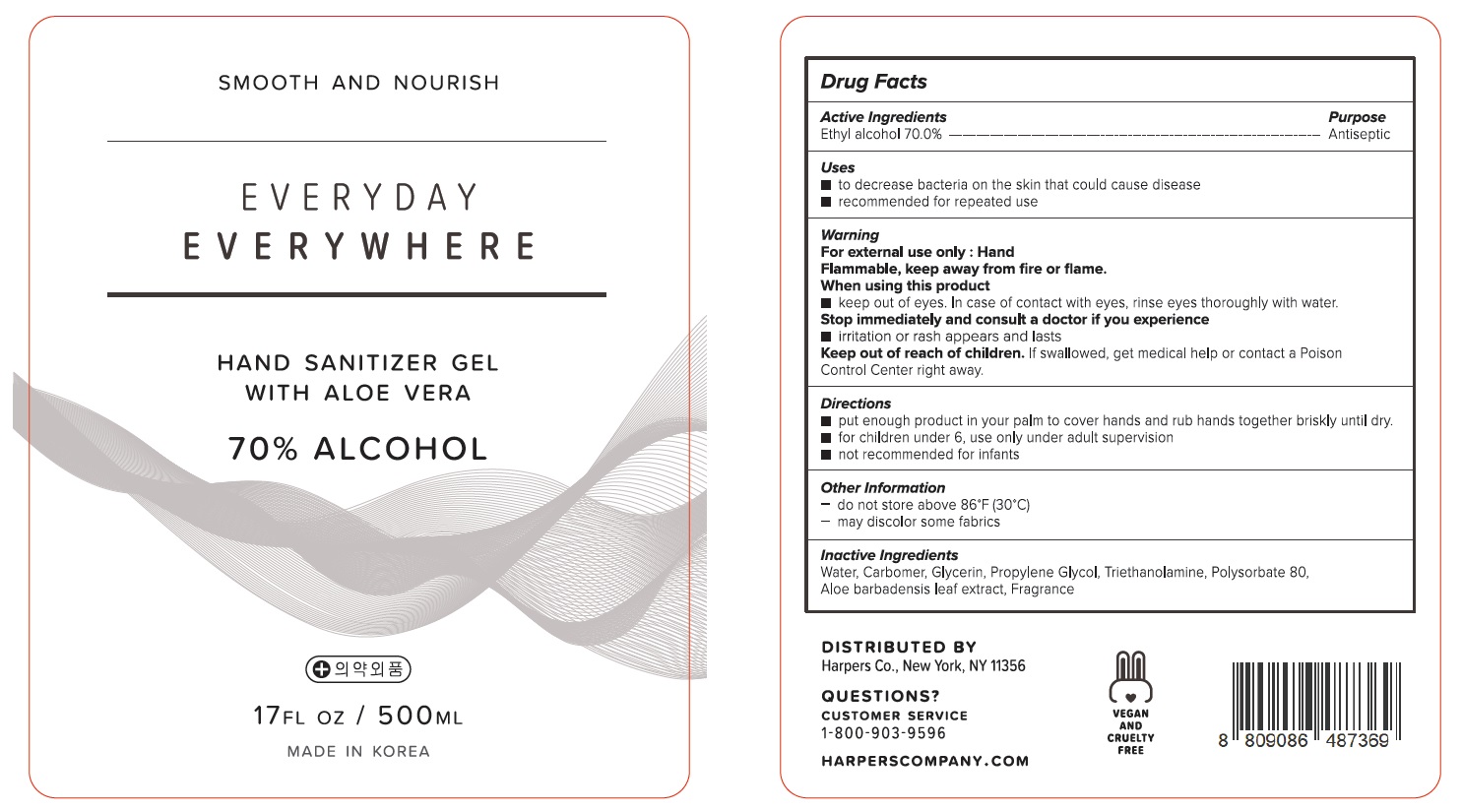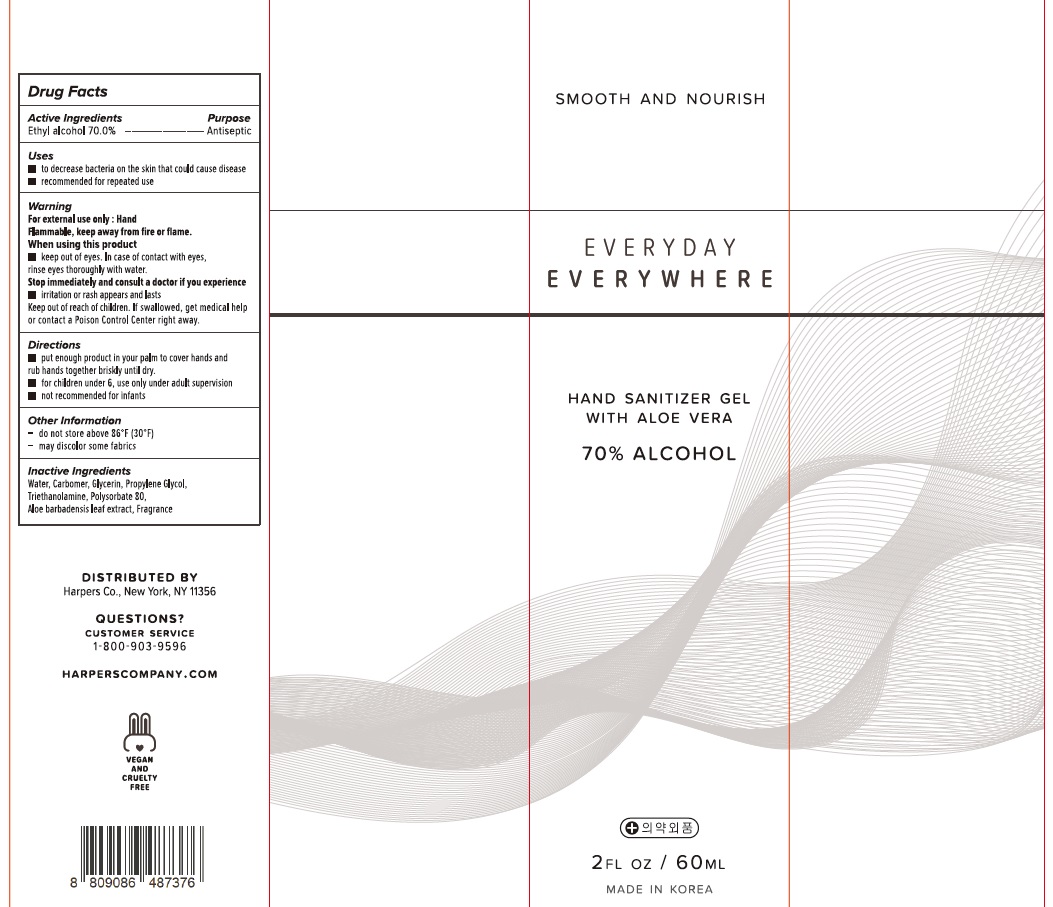 DRUG LABEL: EVERYDAY EVERYWHERE HAND SANITIZER
NDC: 74776-020 | Form: GEL
Manufacturer: C&N COSMETICS CO.,LTD
Category: otc | Type: HUMAN OTC DRUG LABEL
Date: 20200508

ACTIVE INGREDIENTS: ALCOHOL 70 mL/100 mL
INACTIVE INGREDIENTS: Water; CARBOMER HOMOPOLYMER, UNSPECIFIED TYPE; Glycerin; Propylene Glycol; TROLAMINE; Polysorbate 80; ALOE VERA LEAF

ACTIVE INGREDIENT

Active ingredients: Ethyl alcohol 70.0%

INACTIVE INGREDIENT

Inactive ingredients:

Water, Carbomer, Glycerin, Propylene Glycol, Triethanolamine, Polysorbate 80, Aloe barbadensis leaf extract, Fragrance

PURPOSE

Purpose: Antiseptic

WARNINGS

For external use only : Hand
Flammable, keep away from fire or flame.
When using this product
■ keep out of eyes. In case of contact with eyes, rinse eyes thoroughly with water.
Stop immediately and consult a doctor if you experience
■ irritation or rash appears and lasts

Keep out of reach of children. If swallowed, get medical help or contact a Poison Control Center right away.

Uses

■ to decrease bacteria on the skin that could cause disease
■ recommended for repeated use

Directions

■ put enough product in your palm to cover hands and rub hands together briskly until dry.
■ for children under 6, use only under adult supervision
■ not recommended for infants

Other Information

- do not store above 86℉(30℃)
- may discolor some fabrics